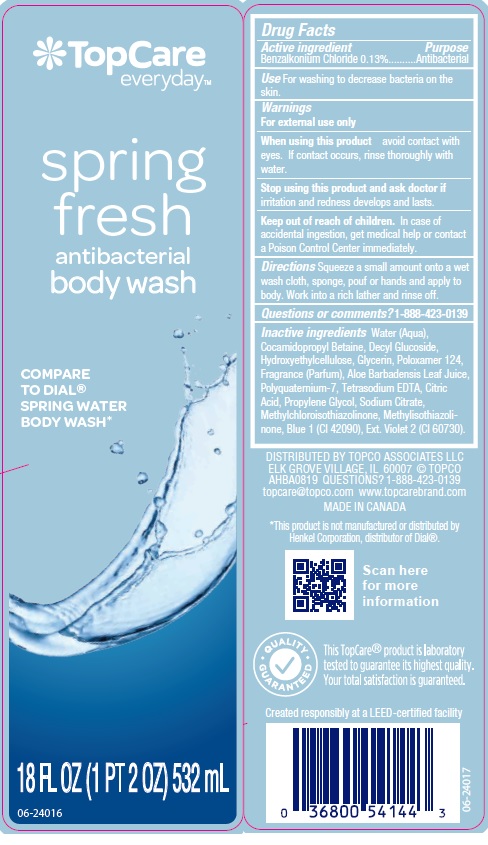 DRUG LABEL: TopCare Everyday Spring Fresh Body Wash
NDC: 36800-895 | Form: LIQUID
Manufacturer: Topco Associates LLC
Category: otc | Type: HUMAN OTC DRUG LABEL
Date: 20191031

ACTIVE INGREDIENTS: BENZALKONIUM CHLORIDE 1.3 mg/1 mL
INACTIVE INGREDIENTS: WATER; COCAMIDOPROPYL BETAINE; DECYL GLUCOSIDE; HYDROXYETHYL CELLULOSE (5000 CPS AT 1%); GLYCERIN; POLOXAMER 124; ALOE VERA LEAF; POLYQUATERNIUM-7 (70/30 ACRYLAMIDE/DADMAC; 1600000 MW); EDETATE SODIUM; CITRIC ACID MONOHYDRATE; PROPYLENE GLYCOL; SODIUM CITRATE; METHYLCHLOROISOTHIAZOLINONE; METHYLISOTHIAZOLINONE; FD&C BLUE NO. 1; EXT. D&C VIOLET NO. 2

Drug Facts

Active ingredient

Benzalkonium Chloride 0.13%

Purpose

Antibacterial

Use

For washing to decrease bacteria on the skin.

Warnings

For external use only.

When using this product

avoid contact with eyes. If contact occurs, rinse thoroughly with water.

Stop using this product and ask a doctor if

irritation and redness develops and lasts.

Keep out of reach of children.

In case of accidental ingestion, get medical help or contact a Poison Control Center immediately.

Directions

Squeeze a small amount onto a wet wash cloth, sponge, pouf or hands and apply to body. Work into a rich lather and rinse off.

Questions or comments?

1-888-423-0139

Inactive ingredients

Water (Aqua), Cocamidopropyl Betaine, Decyl Glucoside, Hydroxyethylcellulose, Glycerin, Poloxamer 124, Fragrance (Parfum), Aloe Barbadensis Leaf Juice, Polyquaternium-7, Tetrasodium EDTA, Citric Acid, Propylene Glycol, Sodium Citrate, Methylchloroisothiazolinone, Methylisothiazolinone, Blue 1 (CI 42090), Ext. Violet 2 (CI 60730).